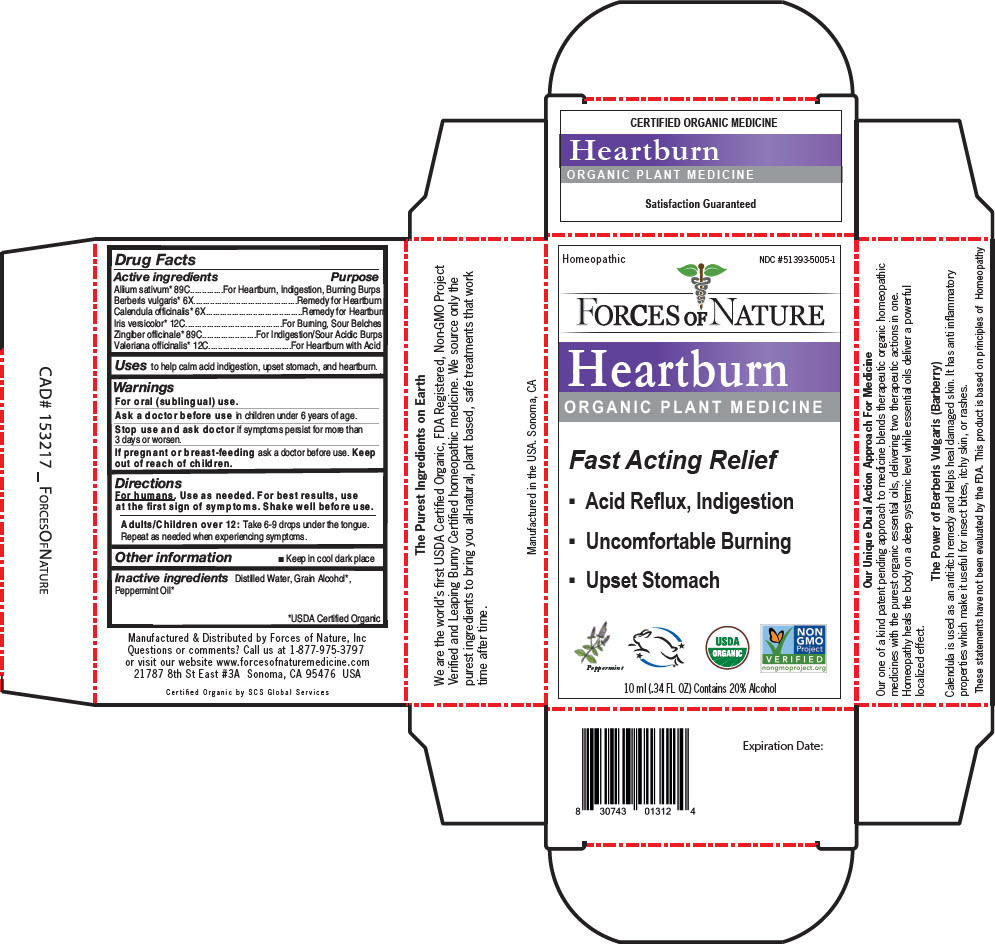 DRUG LABEL: Heartburn
NDC: 51393-5005 | Form: SOLUTION/ DROPS
Manufacturer: Forces of Nature
Category: homeopathic | Type: HUMAN OTC DRUG LABEL
Date: 20210709

ACTIVE INGREDIENTS: Garlic 89 [hp_C]/100 mL; Berberis Vulgaris Root 6 [hp_X]/100 mL; Calendula Officinalis Flowering Top 6 [hp_X]/100 mL; Iris Versicolor Root 12 [hp_C]/100 mL; Ginger 89 [hp_C]/100 mL; Valerian 12 [hp_C]/100 mL
INACTIVE INGREDIENTS: Water; Alcohol; Peppermint Oil

Heartburn

Drug Facts

ACTIVE INGREDIENT

Active ingredients | Purpose
Allium sativum [USDA Certified Organic] 89C | For Heartburn, Indigestion, Burning Burps
Berberis vulgaris 6X | Remedy for Heartburn
Calendula officinalis 6X | Remedy for Heartburn
Iris versicolor 12C | For Burning, Sour Belches
Zingiber officinale 89C | For Indigestion/Sour Acidic Burps
Valeriana officinalis 12C | For Heartburn with Acid

Uses

to help calm acid indigestion, upset stomach, and heartburn.

Warnings

For oral (sublingual) use.

Ask a doctor before use in children under 6 years of age.

Stop use and ask doctor if symptoms persist for more than 3 days or worsen.

PREGNANCY OR BREAST FEEDING

If pregnant or breast-feeding ask a doctor before use.

Keep out of reach of children.

Directions

For humans. Use as needed. For best results, use at the first sign of symptoms. Shake well before use.

Adults/Children over 12

Take 6-9 drops under the tongue. Repeat as needed when experiencing symptoms.

Other information

- Keep in cool dark place

Inactive ingredients

Distilled Water, Grain Alcohol, Peppermint Oil

Questions or comments?

Call us at 1-877-975-3797 or visit our website www.forcesofnaturemedicine.com

Manufactured & Distributed by Forces of Nature, Inc
21787 8th St East #3A Sonoma, CA 95476 USA

PRINCIPAL DISPLAY PANEL - 10 ml Bottle Carton

Homeopathic
NDC #51393-5005-1

FORCES OF NATURE

Heartburn
ORGANIC PLANT MEDICINE

Fast Acting Relief

- Acid Reflux, Indigestion
- Uncomfortable Burning
- Upset Stomach

Peppermint

USDA
ORGANIC

NON
GMO
Project
VERIFIED
nongmoproject.org

10 ml (.34 FL OZ) Contains 20% Alcohol